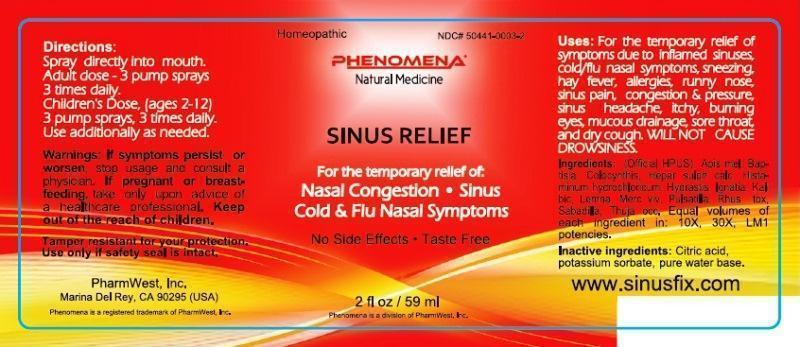 DRUG LABEL: Sinus Relief
NDC: 50441-0003 | Form: LIQUID
Manufacturer: PharmWest Inc.
Category: homeopathic | Type: HUMAN OTC DRUG LABEL
Date: 20140811

ACTIVE INGREDIENTS: APIS MELLIFERA 10 [hp_X]/59 mL; BAPTISIA TINCTORIA ROOT 10 [hp_X]/59 mL; CITRULLUS COLOCYNTHIS FRUIT PULP 10 [hp_X]/59 mL; CALCIUM SULFIDE 10 [hp_X]/59 mL; HISTAMINE DIHYDROCHLORIDE 10 [hp_X]/59 mL; GOLDENSEAL 10 [hp_X]/59 mL; STRYCHNOS IGNATII SEED 10 [hp_X]/59 mL; POTASSIUM DICHROMATE 10 [hp_X]/59 mL; LEMNA MINOR 10 [hp_X]/59 mL; MERCURY 10 [hp_X]/59 mL; PULSATILLA VULGARIS 10 [hp_X]/59 mL; TOXICODENDRON PUBESCENS LEAF 10 [hp_X]/59 mL; SCHOENOCAULON OFFICINALE SEED 10 [hp_X]/59 mL; THUJA OCCIDENTALIS LEAFY TWIG 10 [hp_X]/59 mL
INACTIVE INGREDIENTS: CITRIC ACID MONOHYDRATE; POTASSIUM SORBATE; WATER

Sinus Relief

ACTIVE INGREDIENT

Ingredients: (Official HPUS) Apis mellifica, Baptisia tinctoria, Colocynthis, Hepar sulphuris calcareum, Histaminum hydrochloricum, Hydrastis canadensis, Ignatia amara, Kali bichromicum, Lemna minor, Mercurius vivus, Pulsatilla, Rhus toxicodendron, Sabadilla, Thuja occidentalis. Equal volumes of each ingredient in: 10X, 30X, LM1 potencies.

INACTIVE INGREDIENT

Inactive Ingredients: Citric acid, potassium sorbate, pure water base.

INDICATIONS AND USAGE

Uses: For the temporary relief of symptoms due to inflamed sinuses, cold/flu nasal symptoms, sneezing, hay fever, allergies, runny nose, sinus pain, congestion and pressure, sinus headache, itchy, burning eyes, mucous drainage, sore throat and dry cough. Will not cause drowsiness.

DOSAGE AND ADMINISTRATION

Directions: Spray directly into mouth. Adult dose- 3 pump sprays 3 times daily. Children's Dose, (ages 2-12) 3 pump sprays, 3 times daily. Use additionally as needed.

WARNINGS

Warnings: If symptoms persist or worsen, stop usage and consult a physician. If pregnant or breast-feeding, take only upon advice of a healthcare professional.

Keep out of the reach of children.

OTHER SAFETY INFORMATION

Tamper resistant for your protection. Use only if safety seal is intact.

PURPOSE

Uses: For the temporary relief of symptoms due to inflamed sinuses

- cold/flu nasal symptoms
- sneezing
- hay fever
- allergies
- runny nose
- sinus pain
- congestion and pressure
- sinus headache
- itchy, burning eyes
- mucous drainage
- sore throat
- dry cough

Will not cause drowsiness.